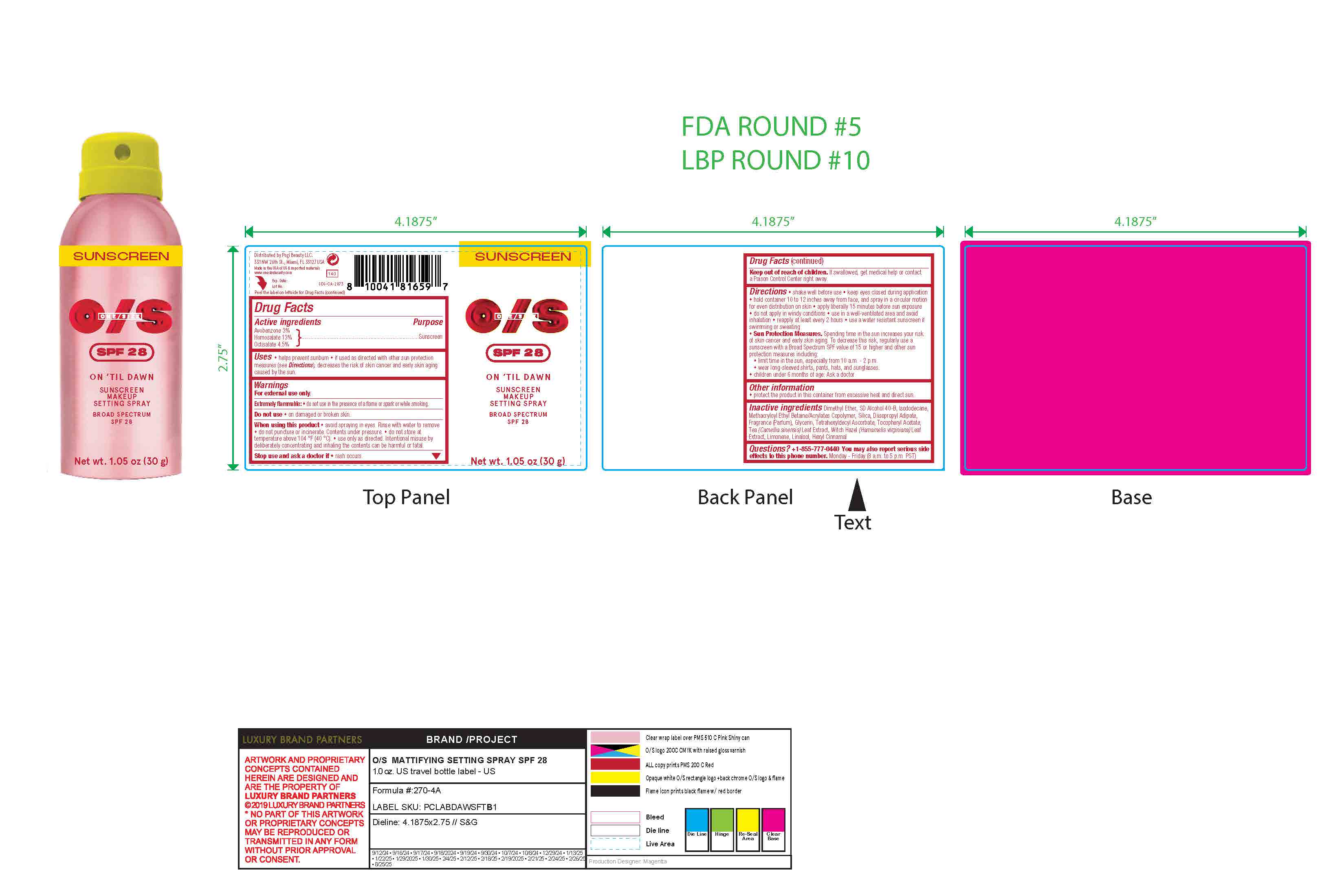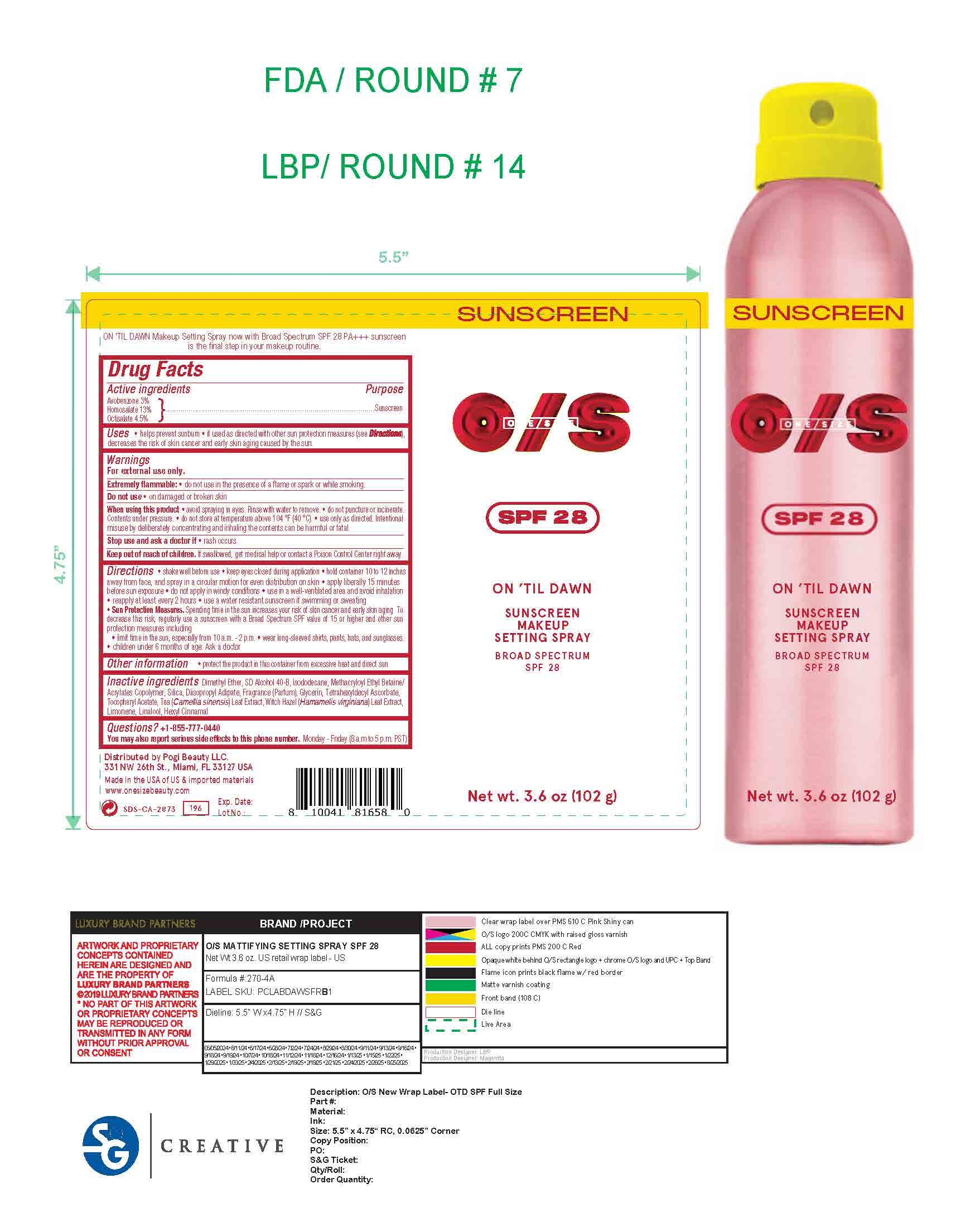 DRUG LABEL: ONE SIZE ON TIL DAWN
NDC: 85307-580 | Form: AEROSOL, SPRAY
Manufacturer: Pogi Beauty LLC
Category: otc | Type: HUMAN OTC DRUG LABEL
Date: 20250917

ACTIVE INGREDIENTS: HOMOSALATE 13 g/100 g; OCTISALATE 4.5 g/100 g; AVOBENZONE 3 g/100 g
INACTIVE INGREDIENTS: FRAGRANCE CLEAN ORC0600327; LIMONENE, (+/-)-; LINALOOL, (+/-)-; HEXYL CINNAMAL; DIMETHYL ETHER; ALCOHOL; SILICON DIOXIDE; DIISOPROPYL ADIPATE; GLYCERIN; TETRAHEXYLDECYL ASCORBATE; CAMELLIA SINENSIS LEAF; ISODODECANE; ALPHA-TOCOPHEROL ACETATE; HAMAMELIS VIRGINIANA LEAF

ONE SIZE ON TIL DAWN MATTIFYING SUNSCREEN MAKEUP SETTING SPRAY

Active Ingredients

Avobenzone 3%

Homosalate 13%

Octisalate 4.5%

Purpose

Sunscreen

Uses

- helps prevent sunburn
- if used as directed with other sun protection measures (see Directions), decreases the risk of skin cancer and early skin aging caused by the sun.

Warnings

For external use only

Extremely flammable

- do not use in the presence of a flame or spark or while smoking.

Do not use

- on damaged or broken skin

When using this product

- avoid apraying in eyes. Rinse with water to remove.
- Do not punctue or incinerate. Contents under pressure.
- Do not store at temperature above 104 F (40 C).
- Use only as directed. Intentional misuse by deliberately concentrating and inhaling the contents can be harmful or fatal.

Stop use and ask a doctor if

- rash occurs.

Keep out of reach of children. If swallowed, get medical help or contact a Poison Control Center right away.

Directions

- shake well before use
- keep eyes closed during application
- hold container 10 to 12 inches away from face, and spray in a circular motion for even distribution on skin
- apply liberally 15 minutes before sun exposure
- do not apply in windy conditions
- use in a well-ventilated area and avoid inhalation
- reapply at least every 2 hours
- use a water-resistant sunscreen if swimming or sweating
- Sun Protection Measures. Spending time in the sun increases your risk of skin cancer and early skin aging. To
  decrease this risk, regularly use a sunscreen with a Broad Spectrum SPF value of 15 or higher and other sun
  protection measures including:
  - limit time in the sun, especially from 10 a.m. - 2 p.m.
  - wear long-sleeved shirts, pants, hats, and sunglasses.
  - children under 6 months of age: Ask a doctor

Other information

- protect the product in this container from excessive heat and direct sun

Inactive ingredients

Dimethyl Ether, SD Alcohol 40-B, Isododecane, Methacryloyl Ethyl Betaine/Acrylates Copolymer, Silica, Diisopropyl Adipate, Fragrance (Parfum), Glycerin, Tetrahexyldecyl Ascorbate, Tocopheryl Acetate, Tea (Camellia sinensis) Leaf Extract, Witch Hazel (Hamamelis virginiana) Leaf Extract, Limonene, Linalool, Hexyl Cinnamal

Questions?

+1-855-777-0440

You may also report serious side effects to this phone number. Monday - Friday (8 a.m to 5 p.m. PST)

Principal display Panel

ONE/SIZE

SPF 28

ON 'TIL DAWN

MATTIFYING

SUNSCREEN

MAKEUP

SETTING SPRAY

BROAD SPECTRUM

SPF 28

Net wt. 3.6 oz (102 g)

Net wt. 1.05 oz (30 g)